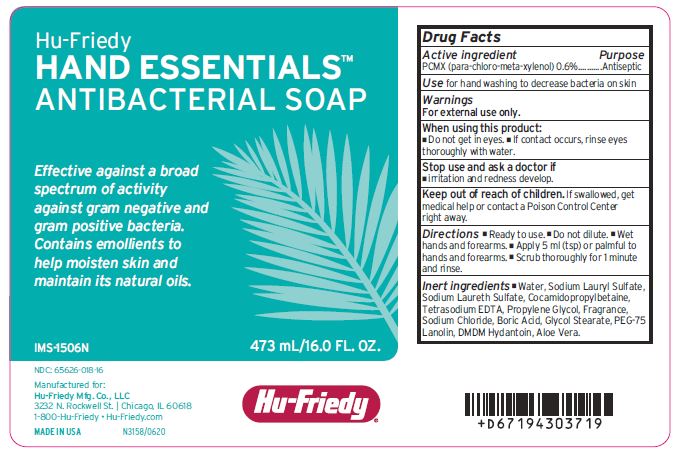 DRUG LABEL: Hand Essentials Antibacterial
NDC: 65626-018 | Form: SOAP
Manufacturer: Hu-Friedy Mfg. Co. LLC
Category: otc | Type: HUMAN OTC DRUG LABEL
Date: 20200604

ACTIVE INGREDIENTS: CHLOROXYLENOL 0.6 g/100 mL
INACTIVE INGREDIENTS: WATER; SODIUM LAURETH SULFATE; COCAMIDOPROPYL BETAINE; EDETATE SODIUM; PROPYLENE GLYCOL; SODIUM CHLORIDE; BORIC ACID; PEG-75 LANOLIN; DMDM HYDANTOIN; SODIUM LAURYL SULFATE; GLYCOL STEARATE; ALOE VERA LEAF

Active ingredient

PCMX (para-chloro-meta-xylenol) 0.6%

Purpose

Antiseptic

Use

for handwashing to decrease bacteria on skin

Warnings

For external use only.

When using this product:

- Do not get in eyes.
- If contact occurs, rinse eyes thoroughly with water.

Stop use and ask a doctor if

- irritation and redness develop.

Keep out of reach of children.

If swallowed, get medical help or contact a Poison Control Center right away.

Directions

- Ready to use.
- Do not dilute.
- Wet hands and forearms.
- Apply 5 ml (tsp) or palmful to hands and forearms.
- Scrub thoroughly for 1 minute and rinse.

Inert ingredients

Water, Sodium Lauryl Sulfate, Sodium Laureth Sulfate, Cocamidopropylbetaine, Tetrasodium EDTA, Propylene Glycol, Fragrance, Sodium Chloride, Boric Acid, Glycol Stearate, PEG-75 Lanolin, DMDM Hydantoin, Aloe Vera.

PACKAGE LABEL

Hu-Friedy

HAND ESSENTIALS

ANTIBACTERIAL SOAP

Effective against a broad

spectrum of activity

against gram negative and

gram positive bacteria.

Contains emollients to

help moisten skin and

maintain its natural oils.

473 ml/16.0 FL. OZ.

NDC: 65626-018-16

Manufactured for:

Hu-Friedy Nfg. Co., LLC

3232 N. Rockwell St. Chicago, IL 60618

1-800-Hu-Friedy Hu-Friedy.com

MADE IN USA

Hu-Friedy